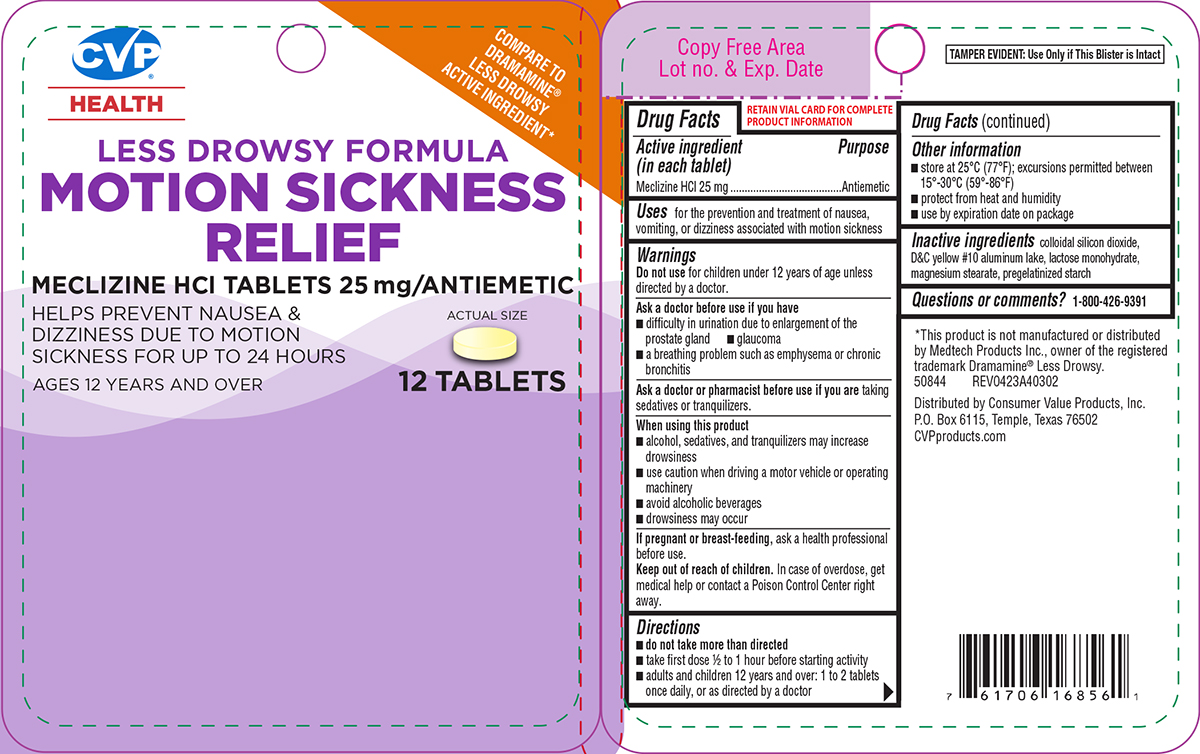 DRUG LABEL: Less Drowsy Formula Motion Sickness Relief
NDC: 57243-403 | Form: TABLET
Manufacturer: Salado Sales, Inc.
Category: otc | Type: HUMAN OTC DRUG LABEL
Date: 20250818

ACTIVE INGREDIENTS: MECLIZINE HYDROCHLORIDE 25 mg/1 1
INACTIVE INGREDIENTS: SILICON DIOXIDE; D&C YELLOW NO. 10 ALUMINUM LAKE; LACTOSE MONOHYDRATE; MAGNESIUM STEARATE; STARCH, CORN

CVP 44-403A

Active ingredient (in each tablet)

Meclizine HCl 25 mg

Purpose

Antiemetic

Uses

for the prevention and treatment of nausea, vomiting, or dizziness associated with motion sickness

Warnings

Do not use

for children under 12 years of age unless directed by a doctor.

Ask a doctor before use if you have

- glaucoma
- difficulty in urination due to enlargement of the prostate gland
- a breathing problem such as emphysema or chronic bronchitis

Ask a doctor or pharmacist before use if you are

taking sedatives or tranquilizers.

When using this product

- alcohol, sedatives, and tranquilizers may increase drowsiness
- drowsiness may occur
- use caution when driving a motor vehicle or operating machinery
- avoid alcoholic beverages

If pregnant or breast-feeding,

ask a health professional before use.

Keep out of reach of children.

In case of overdose, get medical help or contact a Poison Control Center right away.

Directions

- do not take more than directed
- take first dose 1/2 to 1 hour before starting activity
- adults and children 12 years and over: 1 to 2 tablets once daily, or as directed by a doctor

Other information

- store at 25ºC (77ºF); excursions permitted between 15º-30ºC (59º-86ºF)
- protect from heat and humidity
- use by expiration date on package

Inactive ingredients

colloidal silicon dioxide, D&C yellow #10 aluminum lake, lactose monohydrate, magnesium stearate, pregelatinized starch

Questions or comments?

1-800-426-9391

Principal Display Panel

CVP®
Health

COMPARE TO
DRAMAMINE®
LESS DROWSY
ACTIVE INGREDIENT*

LESS DROWSY FORMULA
MOTION SICKNESS
RELIEF
MECLIZINE HCl TABLETS 25 mg/ANTIEMETIC

HELPS PREVENT NAUSEA &
DIZZINESS DUE TO MOTION
SICKNESS FOR UP TO 24 HOURS

AGES 12 YEARS AND OVER

12 TABLETS

ACTUAL SIZE

TAMPER EVIDENT: Use Only if This Blister is Intact

*This product is not manufactured or distributed
by Medtech Products Inc., owner of the registered
trademark Dramamine® Less Drowsy.
50844 REV0423A40302

Distributed by Consumer Value Products, Inc.
P.O. Box 6115, Temple, Texas 76502
CVPproducts.com

CVP 44-403A